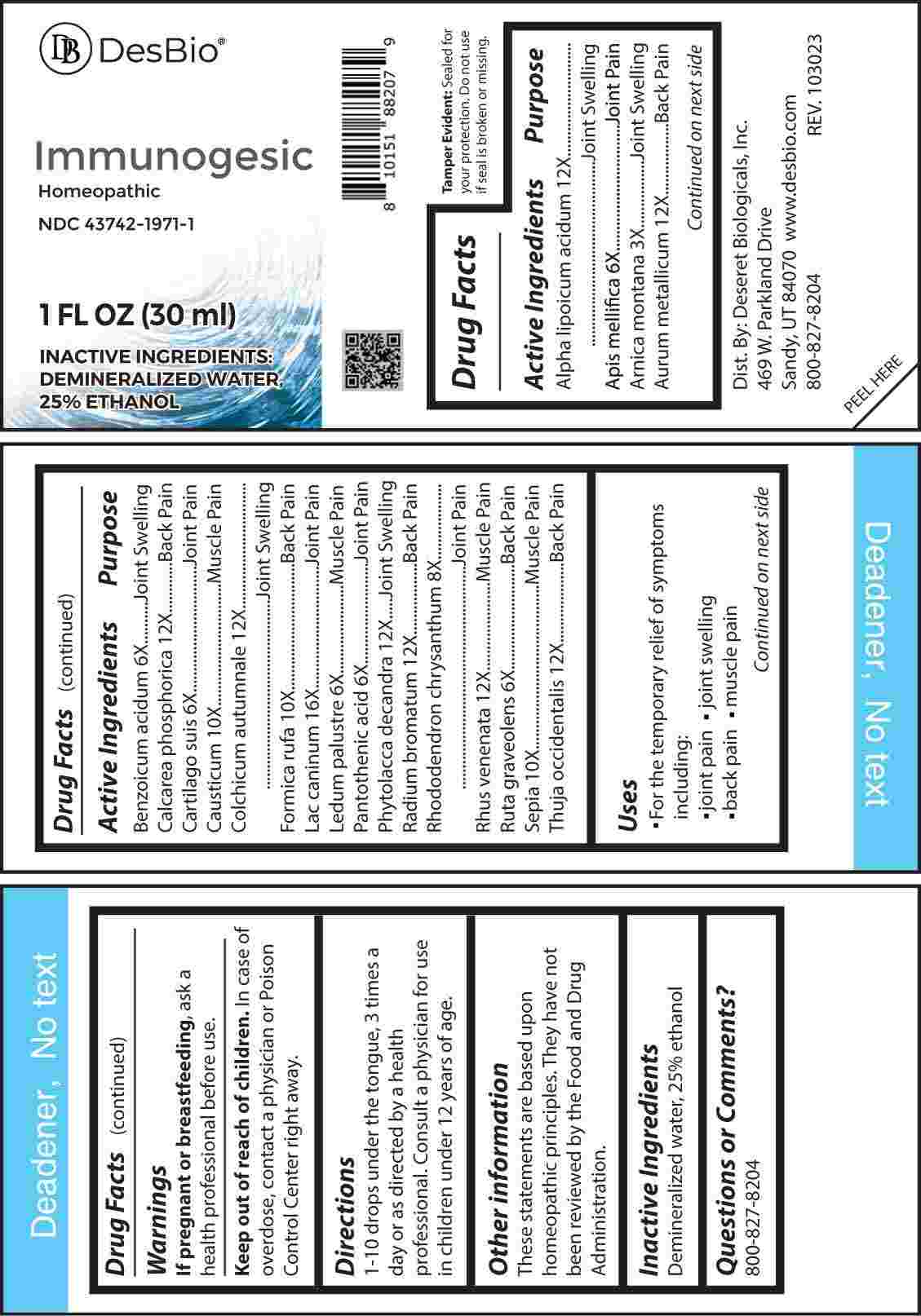 DRUG LABEL: Immunogesic
NDC: 43742-1971 | Form: LIQUID
Manufacturer: Deseret Biologicals, Inc.
Category: homeopathic | Type: HUMAN OTC DRUG LABEL
Date: 20240307

ACTIVE INGREDIENTS: ARNICA MONTANA WHOLE 3 [hp_X]/1 mL; APIS MELLIFERA 6 [hp_X]/1 mL; BENZOIC ACID 6 [hp_X]/1 mL; SUS SCROFA CARTILAGE 6 [hp_X]/1 mL; RHODODENDRON TOMENTOSUM LEAFY TWIG 6 [hp_X]/1 mL; PANTOTHENIC ACID 6 [hp_X]/1 mL; RUTA GRAVEOLENS FLOWERING TOP 6 [hp_X]/1 mL; RHODODENDRON AUREUM LEAF 8 [hp_X]/1 mL; CAUSTICUM 10 [hp_X]/1 mL; FORMICA RUFA 10 [hp_X]/1 mL; SEPIA OFFICINALIS JUICE 10 [hp_X]/1 mL; ALPHA LIPOIC ACID 12 [hp_X]/1 mL; GOLD 12 [hp_X]/1 mL; TRIBASIC CALCIUM PHOSPHATE 12 [hp_X]/1 mL; COLCHICUM AUTUMNALE BULB 12 [hp_X]/1 mL; PHYTOLACCA AMERICANA ROOT 12 [hp_X]/1 mL; RADIUM BROMIDE 12 [hp_X]/1 mL; TOXICODENDRON VERNIX LEAFY TWIG 12 [hp_X]/1 mL; THUJA OCCIDENTALIS LEAFY TWIG 12 [hp_X]/1 mL; CANIS LUPUS FAMILIARIS MILK 16 [hp_X]/1 mL
INACTIVE INGREDIENTS: WATER; ALCOHOL

DRUG FACTS:

ACTIVE INGREDIENTS:

Alpha-Lipoicum Acidum 12X, Apis Mellifica 6X, Arnica Montana 3X, Aurum Metallicum 12X, Benzoicum Acidum 6X, Calcarea Phosphorica 12X, Cartilago Suis 6X, Causticum 10X, Colchicum Autumnale 12X, Formica Rufa 10X, Lac Caninum 16X, Ledum Palustre 6X, Pantothenic Acid 6X, Phytolacca Decandra 12X, Radium Bromatum 12X, Rhododendron Chrysanthum 8X, Rhus Venenata 12X, Ruta Graveolens 6X, Sepia 10X, Thuja Occidentalis 12X.

PURPOSE:

Alpha-Lipoicum Acidum – Joint Swelling, Apis Mellifica – Joint Pain, Arnica Montana – Joint Swelling, Aurum Metallicum – Back Pain, Benzoicum Acidum – Joint Swelling, Calcarea Phosphorica – Back Pain, Cartilago Suis – Joint Pain, Causticum – Muscle Pain, Colchicum Autumnale – Joint Pain, Formica Rufa – Back Pain, Lac Caninum – Joint Pain, Ledum Palustre – Muscle Pain, Pantothenic Acid – Joint Pain, Phytolacca Decandra – Joint Swelling, Radium Bromatum – Back Pain, Rhododendron Chrysanthum – Joint Pain, Rhus Venenata – Muscle Pain, Ruta Graveolens – Back Pain, Sepia – Muscle Pain, Thuja Occidentalis – Back Pain

USES:

• For the temporary relief of symptoms including:

• joint pain • joint swelling • back pain • muscle pain

These statements are based upon homeopathic principles. They have not been reviewed by the Food and Drug Administration.

WARNINGS:

If pregnant or breast-feeding, ask a health professional before use.

Keep out of reach of children. In case of overdose, contact a physician or Poison Control Center right away.

Tamper Evident: Sealed for your protection. Do not use if seal is broken or missing.

KEEP OUT OF REACH OF CHILDREN:

In case of overdose, contact a physician or Poison Control Center right away.

DIRECTIONS:

1-10 drops under the tongue, 3 times a day or as directed by a health professional. Consult a physician for use in children under 12 years of age.

INACTIVE INGREDIENTS:

Demineralized water, 25% ethanol.

QUESTIONS:

Dist. By: Deseret Biologicals, Inc.

469 W. Parkland Drive

Sandy, UT 84070

www.desbio.com

800-827-8204

PACKAGE LABEL DISPLAY:

Des Bio

Immunogesic

Homeopathic

NDC 43742-1971-1

1 FL OZ (30 ml)